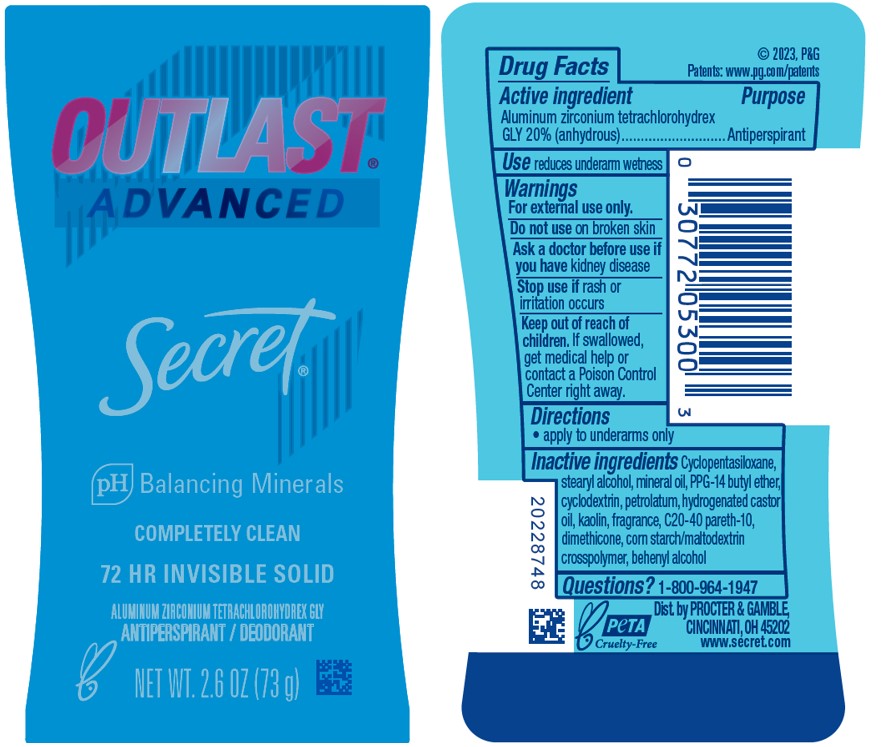 DRUG LABEL: Secret Outlast Advanced Invisible Completely Clean
NDC: 69423-637 | Form: STICK
Manufacturer: The Procter & Gamble Manufacturing Company
Category: otc | Type: HUMAN OTC DRUG LABEL
Date: 20250826

ACTIVE INGREDIENTS: ALUMINUM ZIRCONIUM TETRACHLOROHYDREX GLY 20 g/100 g
INACTIVE INGREDIENTS: CYCLODEXTRINS; STEARYL ALCOHOL; MINERAL OIL; DIMETHICONE; KAOLIN; PETROLATUM; HYDROGENATED CASTOR OIL; PPG-14 BUTYL ETHER; C20-40 PARETH-10; BEHENYL ALCOHOL; CYCLOPENTASILOXANE

Secret® Outlast™ Advanced Invisible Solid Completely Clean

Drug Facts

Active ingredient

Aluminum zirconium tetrachlorohydrex Gly 20% (anhydrous)

Purpose

Antiperspirant

Use

reduces underarm wetness

Warnings

For external use only.

Do not use on broken skin

Ask a doctor before use if you have kidney disease

Stop use if rash or irritation occurs

Keep out of reach of children. If swallowed, get medical help or contact a Poison Control Center right away.

Directions

apply to underarms only

Inactive ingredients

Cyclopentasiloxane, stearyl alcohol, mineral oil, PPG-14 butyl ether, cyclodextrin, petrolatum, hydrogenated castor oil, kaolin, fragrance, C20-40 pareth-10, dimethicone, corn starch/maltodextrin crosspolymer, behenyl alcohol

Questions?

1-800-964-1947

Dist. by PROCTER & GAMBLE,
CINCINNATI, OH 45202.

PRINCIPAL DISPLAY PANEL - 73 g Cylinder Label

OUTLAST™

ADVANCED

Secret®

pH Balancing Minerals

COMPLETELYL CLEAN

72 HR INVISIBLE SOLID

ALUMINUM ZIRCONIUM TETRACHLOROHYDREX GLY
ANTIPERSPIRANT/DEODORANT

NET WT. 2.6 OZ (73 g)